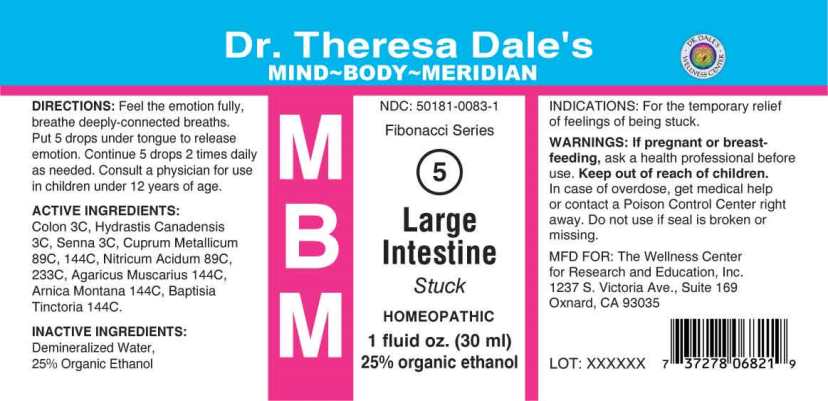 DRUG LABEL: MBM 5 Large Intestine
NDC: 50181-0083 | Form: LIQUID
Manufacturer: The Wellness Center
Category: homeopathic | Type: HUMAN OTC DRUG LABEL
Date: 20250606

ACTIVE INGREDIENTS: SUS SCROFA COLON 3 [hp_C]/1 mL; GOLDENSEAL 3 [hp_C]/1 mL; SENNA LEAF 3 [kp_C]/1 mL; COPPER 89 [hp_C]/1 mL; NITRIC ACID 89 [hp_C]/1 mL; AMANITA MUSCARIA FRUITING BODY 144 [hp_C]/1 mL; ARNICA MONTANA WHOLE 144 [hp_C]/1 mL; BAPTISIA TINCTORIA WHOLE 144 [hp_C]/1 mL
INACTIVE INGREDIENTS: WATER; ALCOHOL

DRUG FACTS:

ACTIVE INGREDIENTS:

Colon (Suis) 3C, Hydrastis Canadensis 3C, Senna (Cassia Angustifolia) 3C, Cuprum Metallicum 89C, 144C, Nitricum Acidum 89C, 233C, Agaricus Muscarius 144C, Arnica Montana 144C, Baptisia Tinctoria 144C.

INDICATIONS:

For the temporary relief of feelings of being stuck.

WARNINGS:

If pregnant or breast-feeding, ask a health professional before use. Keep out of reach of children. In case of overdose, get medical help or contact a Poison Control Center right away. Do not use if seal is broken or missing.

KEEP OUT OF REACH OF CHILDREN:

In case of overdose, get medical help or contact a Poison Control Center right away.

DIRECTIONS:

Feel the emotion fully, breathe deeply-connected breaths. Put 5 drops under tongue to release emotion. Continue 5 drops 2 times daily as needed. Consult a physician for use in children under 12 years of age.

INDICATIONS:

For the temporary relief of feelings of being stuck.

INACTIVE INGREDIENTS:

Demineralized Water, 25% Organic Ethanol

QUESTIONS:

MFD FOR: The Wellness Center

for Research and Education, Inc.

1237 S. Victoria Ave., Suite 169

Oxnard, CA 93035

PACKAGE LABEL DISPLAY:

Dr. Theresa Dale's

MIND BODY MERIDIAN

NDC: 50181-0083-1

Fibonacci Series

5

Large

Intestine

Stuck

HOMEOPATHIC

1 fluid oz. (30 ml)